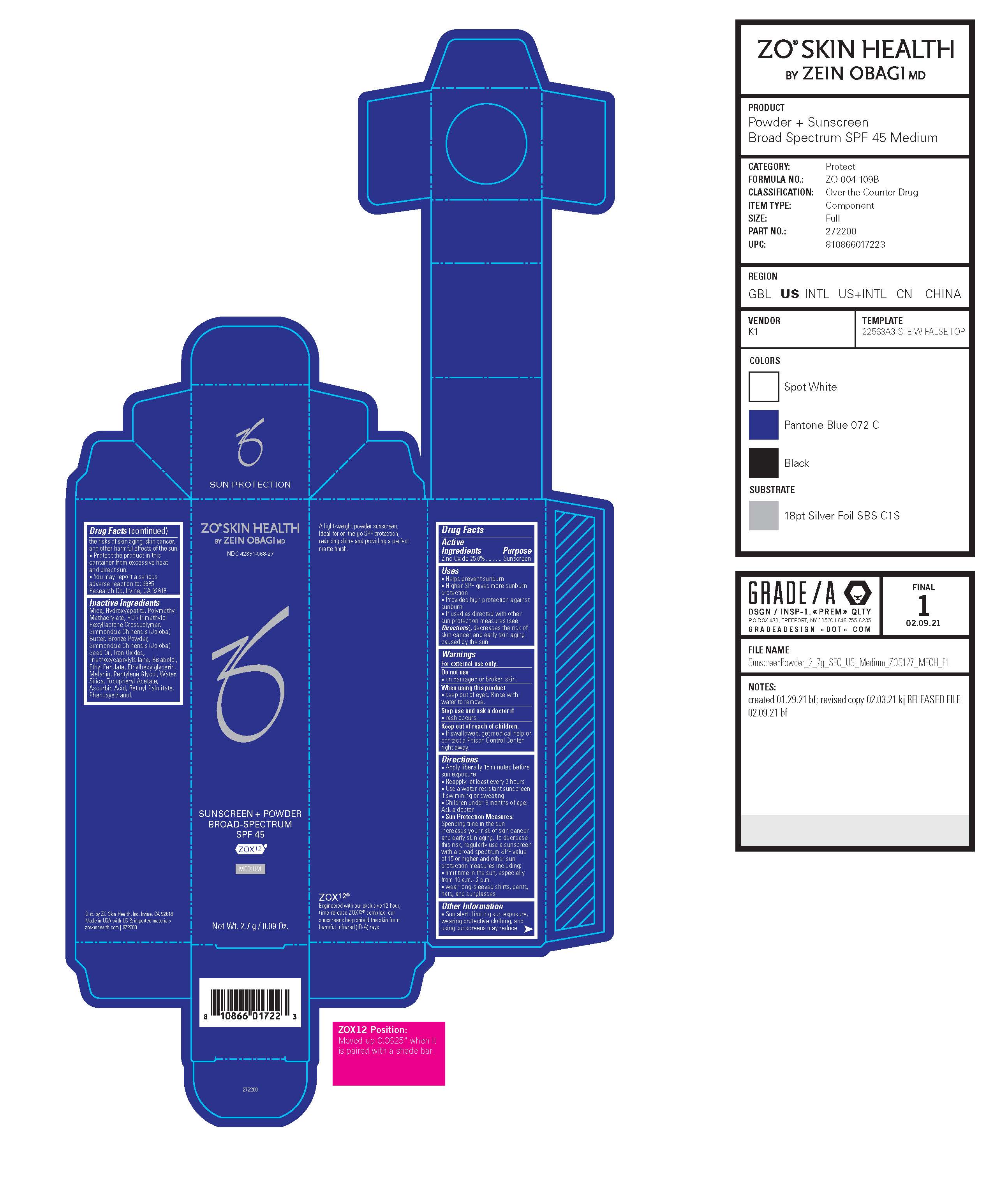 DRUG LABEL: ZO Skin Health Sunscreen Plus Powder Broad-Spectrum SPF 45
NDC: 42851-068 | Form: POWDER
Manufacturer: ZO Skin Health, Inc.
Category: otc | Type: HUMAN OTC DRUG LABEL
Date: 20241112

ACTIVE INGREDIENTS: ZINC OXIDE 0.675 mg/2.7 g
INACTIVE INGREDIENTS: ASCORBIC ACID; JOJOBA BUTTER; COPPER; JOJOBA OIL; TRIETHOXYCAPRYLYLSILANE; PENTYLENE GLYCOL; SILICON DIOXIDE; VITAMIN A PALMITATE; ETHYLHEXYLGLYCERIN; TRIBASIC CALCIUM PHOSPHATE; FERRIC OXIDE RED; .ALPHA.-TOCOPHEROL ACETATE; HEXAMETHYLENE DIISOCYANATE/TRIMETHYLOL HEXYLLACTONE CROSSPOLYMER; ETHYL FERULATE; MICA; POLY(METHYL METHACRYLATE; 450000 MW); PHENOXYETHANOL

ZO ® Skin Health Sunscreen + Powder Broad-Spectrum SPF 45 (Medium)
National Drug Code 42851-068-27

Drug Facts

Active Ingredients

Active Ingredents | Purpose
Zinc Oxide 25.0% | Sunscreen

Purpose Sunscreen

Uses

- Helps prevent sunburn
- Higher SPF gives more sunburn protection
- Provides high protection against sunburn
- If used as directed with other sun protection measures (see Directions), decreases the risk of skin cancer and early skin aging caused by the sun

Warnings

For external use only.

Do not use

- on damaged or broken skin.

When using this product

- keep out of eyes. Rinse with water to remove.

Stop use and ask a doctor if

- rash occurs.

Keep out of reach of children.

- If swallowed, get medical help or contact a Poison Control Center right away.

Directions

- Apply liberally 15 minutes before sun exposure
- Reapply: at least every 2 hours
- Use a water-resistant sunscreen if swimming or sweating
- Children under 6 months of age: Ask a doctor
- Sun Protection Measures. Spending time in the sun increases your risk of skin cancer and early skin aging. To decrease this risk, regularly use a sunscreen with a broad spectrum SPF value of 15 or higher and other sun protection measures including: - limit time in the sun, especially from 10 a.m.- 2 p.m. - wear long-sleeved shirts, pants, hats, and sunglasses.

Other Information

- Sun alert: Limiting sun exposure, wearing protective clothing, and using sunscreens may reduce the risks of skin aging, skin cancer, and other harmful effects of the sun.

STORAGE AND HANDLING

- Protect the product in this container from excessive heat and direct sun.

QUESTIONS

- You may report a serious adverse reaction to: 9685 Research Dr., Irvine, CA 92618

Inactive Ingredients

Mica, Hydroxyapatite, Polymethyl Methacrylate, HDI/Trimethylol Hexyllactone Crosspolymer, Simmondsia Chinensis (Jojoba) Butter, Bronze Powder, Simmondsia Chinensis (Jojoba) Seed Oil, Iron Oxides, Triethoxycaprylylsilane, Bisabolol, Ethyl Ferulate, Ethylhexylglycerin, Melanin, Pentylene Glycol, Water, Silica, Tocopheryl Acetate, Ascorbic Acid, Retinyl Palmitate, Phenoxyethanol.

Principal Display Panel

ZO® SKIN HEALTH
BY ZEIN OBAGI MD

NDC 42851-068-27

SUNSCREEN + POWDER
BROAD-SPECTRUM
SPF 45

ZOX12®

MEDIUM

Net Wt. 2.7 g / 0.09 Oz.